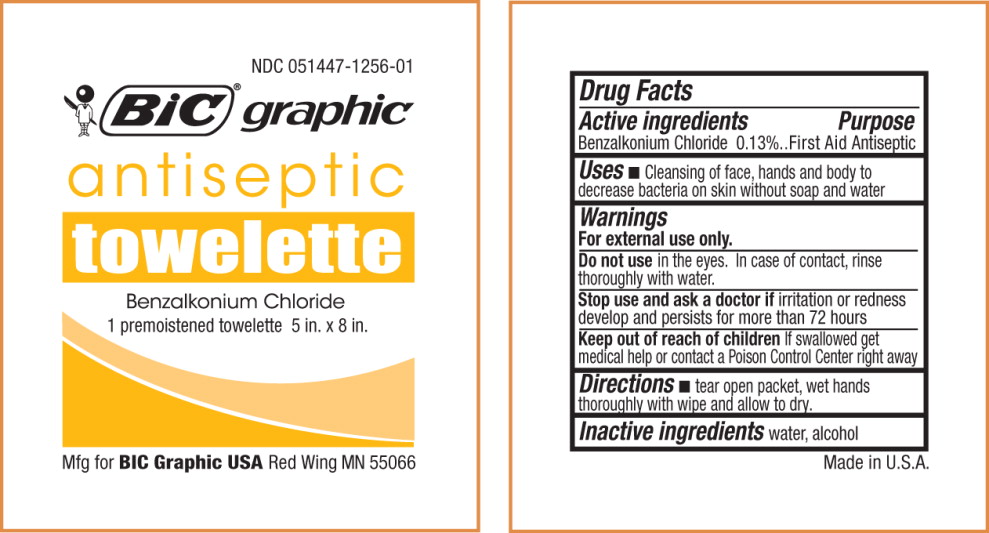 DRUG LABEL: BZK
NDC: 51447-1256 | Form: LIQUID
Manufacturer: BIC Graphic USA Manufacturing Co, Inc.
Category: otc | Type: HUMAN OTC DRUG LABEL
Date: 20140716

ACTIVE INGREDIENTS: benzalkonium chloride 0.0013 g/1 g
INACTIVE INGREDIENTS: water; alcohol

Active ingredients

Benzalkonium Chloride 0.13%

Purpose

First Aid Antiseptic

Uses

- Antiseptic cleansing of face, hands and body to decrease bacteria on skin without soap and water

Warnings

For external use only.

Do not use in the eyes. If this happens, rinse thoroughly with water.

Stop use and ask a doctor if irritation or redness develop and persists for more than 72 hours

Keep out of reach of children If swallowed get medical help or contact a Poison Control Center right away

Directions

- Tear open packet, unfold and use as a washcloth. Allow hands to dry without wiping.

Inactive ingredients

purified water, alcohol

PACKAGE LABEL

NDC 051447-1256-01

BiC graphic

Antiseptic

Towelette

Benzalkonium Chloride

1 premoistened towelette 5 in. x 8 in.

Mfg for BICGraphic Red Wing MN 55066 Made in U.S.A.